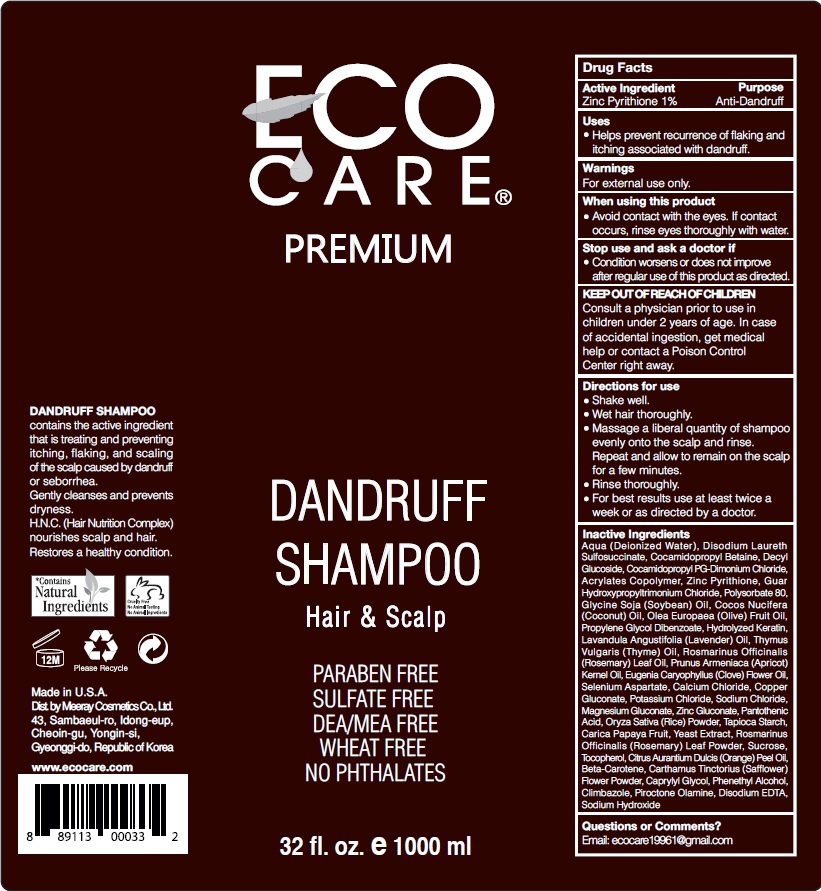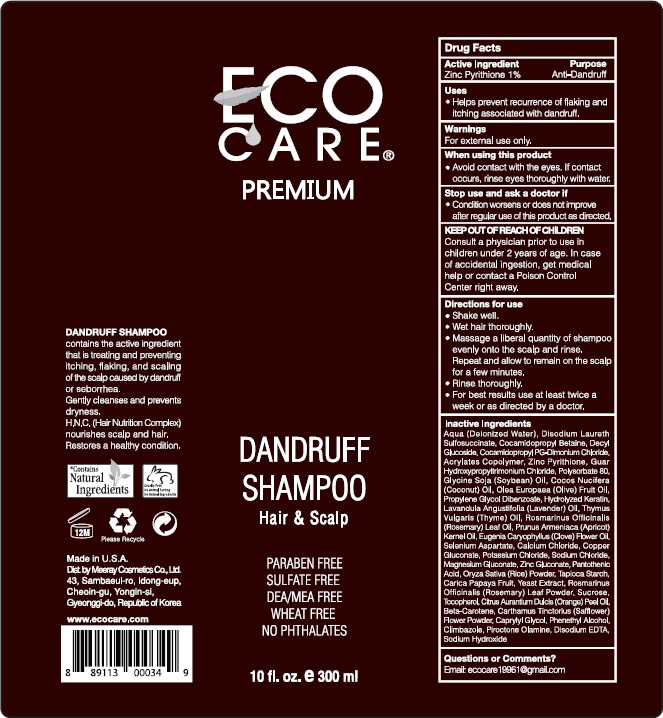 DRUG LABEL: Anti-Dandruff
NDC: 83080-121 | Form: SHAMPOO
Manufacturer: MEERAY COSMETICS CO., LTD.
Category: otc | Type: HUMAN OTC DRUG LABEL
Date: 20230227

ACTIVE INGREDIENTS: PYRITHIONE ZINC 10 mg/100 mL
INACTIVE INGREDIENTS: SOYBEAN OIL; COCONUT OIL; POTASSIUM CHLORIDE; ORYZA SATIVA WHOLE; ROSMARINUS OFFICINALIS FLOWER; CAPRYLYL GLYCOL; DECYL GLUCOSIDE; GUAR HYDROXYPROPYLTRIMONIUM CHLORIDE (1.7 SUBSTITUENTS PER SACCHARIDE); PANTOTHENIC ACID; OLIVE OIL; WATER; ROSMARINUS OFFICINALIS FLOWERING TOP OIL; YEAST; SODIUM HYDROXIDE; DISODIUM 1-(LAURETH-2) SULFOSUCCINATE; PROPYLENE GLYCOL DIBENZOATE; SODIUM CHLORIDE; 4-METHYLPHENETHYL ALCOHOL; STARCH, TAPIOCA; CARICA PAPAYA WHOLE; DISODIUM EDTA-COPPER; SUCROSE; TOCOPHEROL; PIROCTONE OLAMINE; COCAMIDOPROPYL PG-DIMONIUM CHLORIDE; AMINO ACIDS, HAIR KERATIN; ACRYLATE/ISOBUTYL METHACRYLATE/N-TERT-OCTYLACRYLAMIDE COPOLYMER (75000 MW); MAGNESIUM GLUCONATE; ZINC GLUCONATE; MYRTUS COMMUNIS LEAF; LAVANDULA ANGUSTIFOLIA FLOWER; THYMUS VULGARIS LEAF; BETA CAROTENE; SAFFLOWER; SALVIA OFFICINALIS FLOWERING TOP; CITRIC ACID ACETATE; PROPANEDIAMINETETRAACETIC ACID; COCAMIDOPROPYL BETAINE; POLYSORBATE 80; CALCIUM CHLORIDE; COPPER GLUCONATE; SUPEROXIDE DISMUTASE (SACCHAROMYCES CEREVISIAE); MANGANESE GLUCONATE; OLEA EUROPAEA FRUIT VOLATILE OIL; ORANGE PEEL; PRUNUS ARMENIACA LEAF; CLOVE LEAF OIL; CLIMBAZOLE

Ecocare Dandruff Shampoo

Drug Facts

Active Ingredients Purpose

Zinc Pyrithione 1.00 %.........................................................Anti-Dandruff

Purpose

Uses: Helps prevent recurrence of flaking and itching associated with dandruff.

Warnings

FOR EXTERNAL USE ONLY

When using this product

Avoid contact with the eyes. If contact occurs, rinse eyes thoroughly with water.

Stop use and ask a doctor if condition worsens or does not improve after regular use of this product as directed.

Keep out of reach of children

Dosage and Administration

- Shake well.
- Wet hair thoroughly.
- Massage a liberal quantity of shampoo evenly onto the scalp and rinse. Repeat and allow to remain on the scalp for a few minutes.
- Rinse throroughly.
- For best results use at least twice a week or as directed by a doctor.

Ask a doctor

Condition worsens or does not improve after regular use of this product as directed.

Do Not Use

Condition worsens or does not improve after regular use of this product as directed.

Inactive Ingredients

Aqua (Deionized Water), Decyl Glucoside, Lauryl Glucoside, Coco Glucoside, Hydrolyzed Soy Protein, Guar Hydroxypropyltrimonium Chloride, Hydrolyzed Keratin, Tocopherol, Pantothenic Acid, Saccharomyces/Selenium Ferment, Calcium Chloride, Copper Gluconate, Potassium Chloride, Managanese Gluconate, Magnesium Gluconate, Zinc Gluconate, Sodium Chloride, Olea Europaea Fruit Oil, Myrtus Comunis Oil, Lavandula Angustifolia Oil, Thymus Vulgaris Oil, Rosmarinus Officinalis Leaf Oil, Prunus Armeniaca Kernal Oil, Eugenia Caryophyllus Flower Oil, Oryza Sativa Powder, Tapioca Starch, Carica Papayan Fruit, Yeast Extract, Rosmarinus Officinalis Leaf Powder, Salvia Officinalis Leaf Extract, Sucrose, Phenethyl Alcohol, Caprylyl Glycol, Citric Acid, Tetrasodium EDTA, Essential Oils Blend

Indications

Helps prevent recurrance of flaking and itching associated with dandruff.